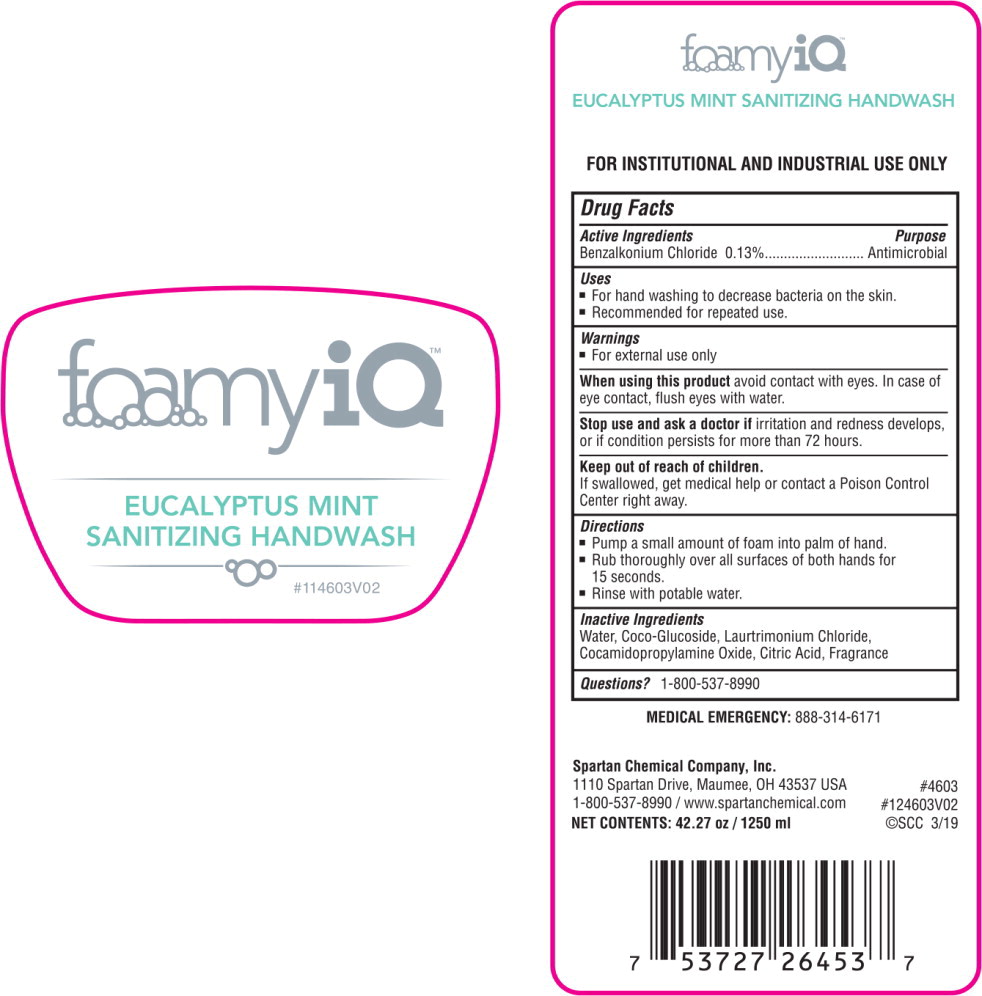 DRUG LABEL: FoamyIQ Eucalyptus Mint Sanitizing Handwash
NDC: 64009-201 | Form: SOAP
Manufacturer: Spartan Chemical Company, Inc.
Category: otc | Type: HUMAN OTC DRUG LABEL
Date: 20251007

ACTIVE INGREDIENTS: BENZALKONIUM CHLORIDE 1.3 g/1 L
INACTIVE INGREDIENTS: WATER; COCO GLUCOSIDE; LAURTRIMONIUM CHLORIDE; CITRIC ACID MONOHYDRATE; CAPRYLYL/CAPRYL GLUCOSIDE; MYRISTAMIDOPROPYLAMINE OXIDE

Drug Facts

Active Ingredients

Benzalkonium Chloride 0.13%

Purpose

Antimicrobial

Uses

- For hand washing to decrease bacteria on the skin.
- Recommended tor repeated use.

Warnings

- For external use only

When using this product avoid contact with eyes. In case of eye contact, flush eyes with water.

Stop use and ask a doctor if irritation and redness develops, or if condition persists for more than 72 hours.

Keep out of reach of children.

If swallowed, get medical help or contact a Poison Control Center right away.

Directions

- Pump a small amount of foam into palm of hand.
- Rub thoroughly over all surfaces of both hands for 15 seconds.
- Rinse with potable water.

Inactive Ingredients

Water, Coco-Glucoside, Laurtrimonium Chloride, Cocamidopropylamine Oxide, Citric Acid

Questions?

1-800-537-8990

Principal Display Panel - 1.25 L Container Label

foamy iQ™

EUCALYPTUS MINT
SANITIZING HANDWASH

#114603V02